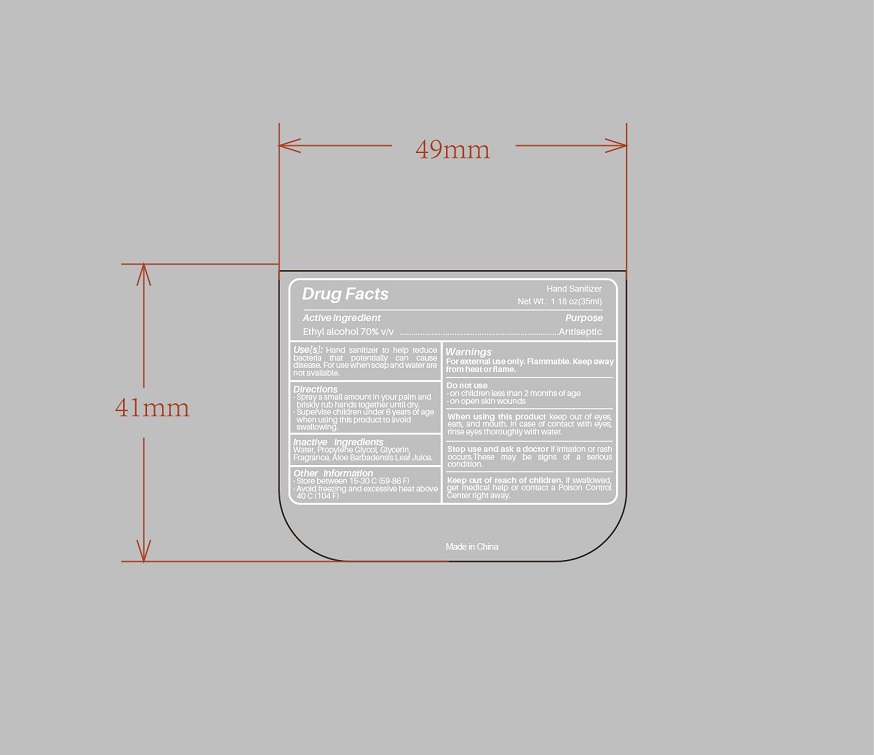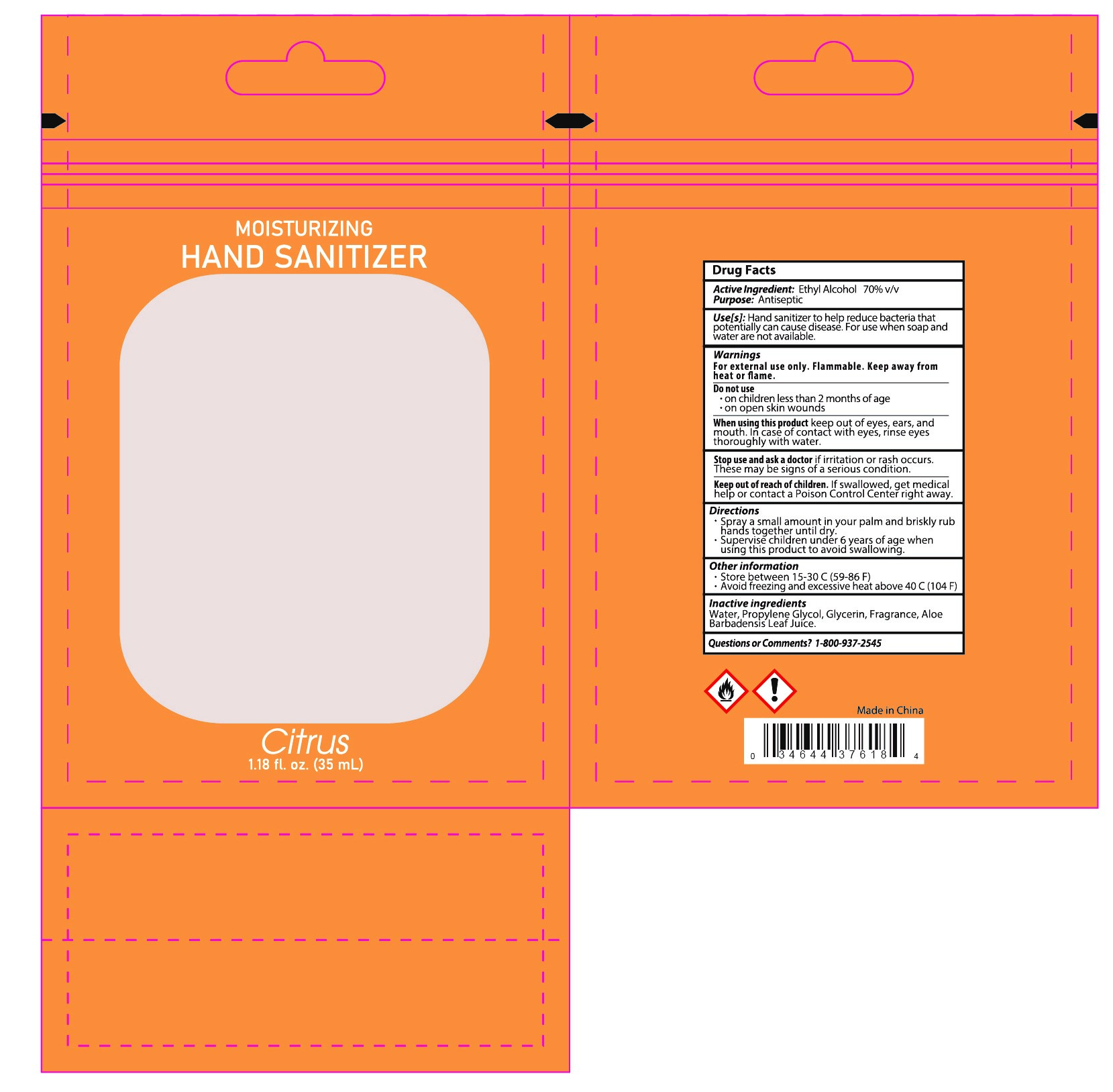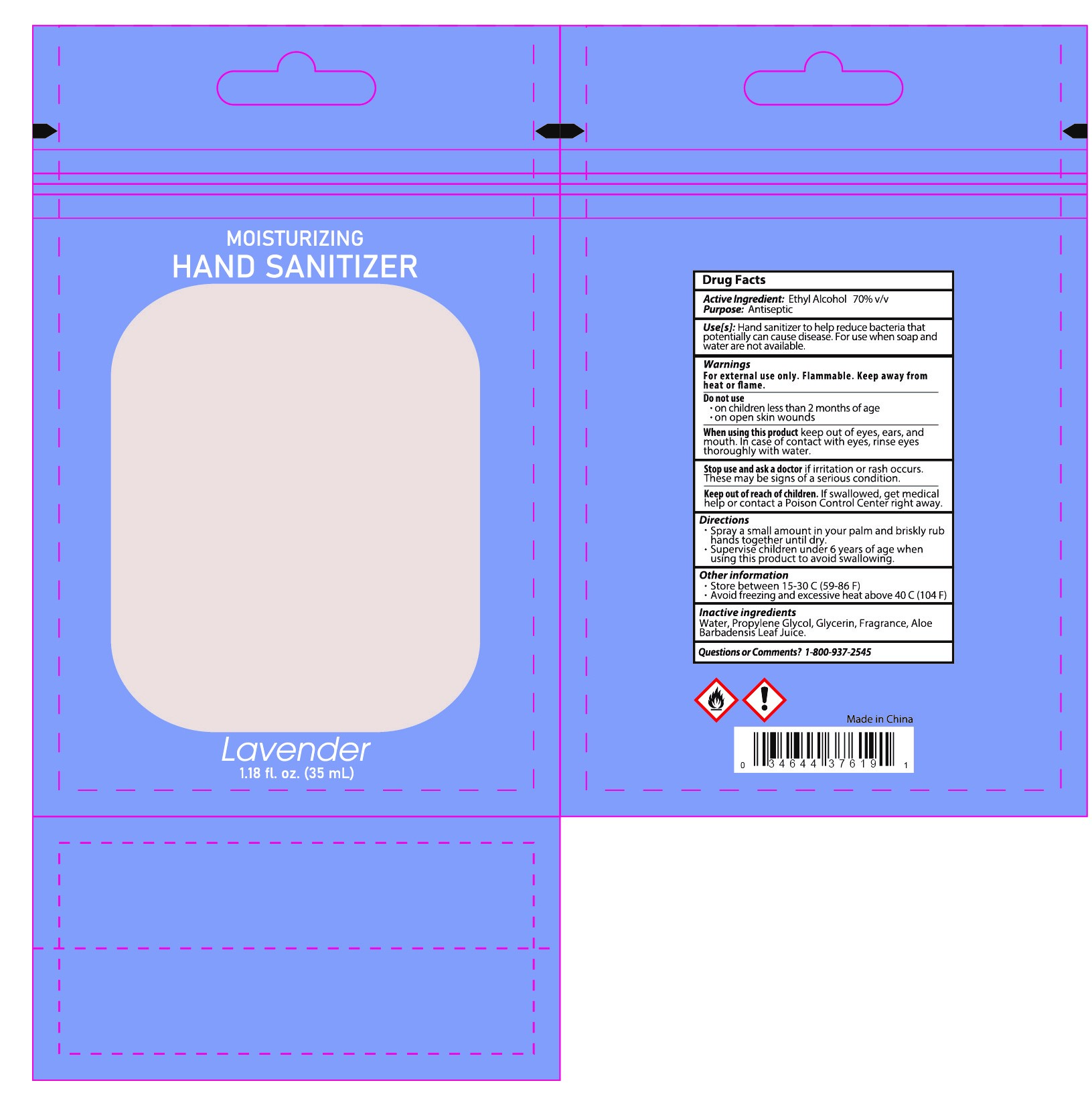 DRUG LABEL: Hand Sanitizer
NDC: 87001-005 | Form: SPRAY
Manufacturer: HAIAN KANGRUI TEXTILE CO., LTD.
Category: otc | Type: HUMAN OTC DRUG LABEL
Date: 20251125

ACTIVE INGREDIENTS: ALCOHOL 70 mL/100 mL
INACTIVE INGREDIENTS: GLYCERIN; PROPYLENE GLYCOL; ALOE BARBADENSIS LEAF JUICE; WATER

87001-005-01

Active Ingredient

Ethyl Alcohol 70% V/V

Purpose

Antiseptic

Use(s)

Hand sanitizer to help reducebacteria that potentially can causedisease. For use when soap and water arenot available.

Warnings

For external use only.Flammable. Keep away from fire and flame.

Do not use

·on children less than 2 months of age

·on open skin wounds

When using this product，

do not use in or near the eyes.In case of contact，rinse eyes thoroughly with water.

Stop use and ask a doctor

if irritation or rashoccurs These.

may be signs of a seriouscondition.

Keep out of reach of children.

If swallowed, get medical help or contact a Poison Control Center right away.

Directions

Spray a small amount in your palm and briskly rub hands together until dry.

Supeivise children under 6 years of age when using this product to avoid swallowing.

Inactive ingredients

Water，Propylene Glycol，Glycerin，Fragrance，Aloe Barbadensis Leaf Juice